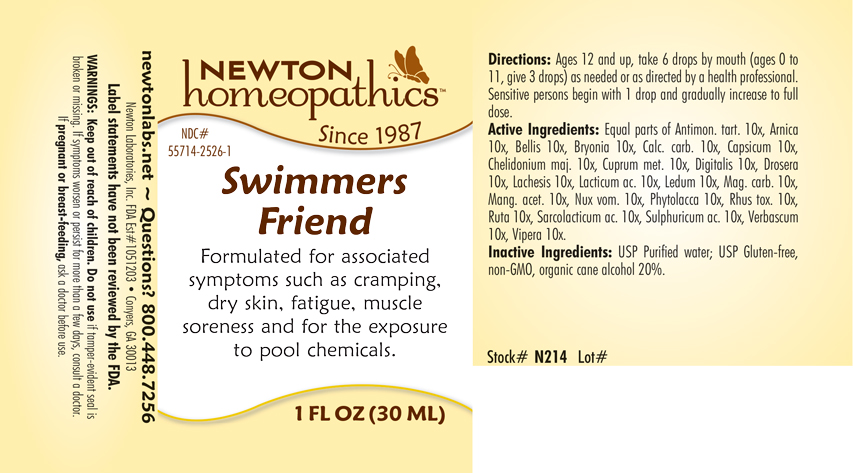 DRUG LABEL: Swimmers Friend
NDC: 55714-2526 | Form: LIQUID
Manufacturer: Newton Laboratories, Inc.
Category: homeopathic | Type: HUMAN OTC DRUG LABEL
Date: 20250210

ACTIVE INGREDIENTS: ANTIMONY POTASSIUM TARTRATE 10 [hp_X]/1 mL; BELLIS PERENNIS 10 [hp_X]/1 mL; BRYONIA ALBA ROOT 10 [hp_X]/1 mL; OYSTER SHELL CALCIUM CARBONATE, CRUDE 10 [hp_X]/1 mL; CAPSICUM 10 [hp_X]/1 mL; CHELIDONIUM MAJUS 10 [hp_X]/1 mL; COPPER 10 [hp_X]/1 mL; DIGITALIS 10 [hp_X]/1 mL; DROSERA ANGLICA 10 [hp_X]/1 mL; LACHESIS MUTA VENOM 10 [hp_X]/1 mL; LACTIC ACID, DL- 10 [hp_X]/1 mL; RHODODENDRON TOMENTOSUM LEAFY TWIG 10 [hp_X]/1 mL; MAGNESIUM CARBONATE 10 [hp_X]/1 mL; MANGANESE ACETATE TETRAHYDRATE 10 [hp_X]/1 mL; STRYCHNOS NUX-VOMICA SEED 10 [hp_X]/1 mL; PHYTOLACCA AMERICANA ROOT 10 [hp_X]/1 mL; TOXICODENDRON PUBESCENS LEAF 10 [hp_X]/1 mL; RUTA GRAVEOLENS FLOWERING TOP 10 [hp_X]/1 mL; LACTIC ACID, L- 10 [hp_X]/1 mL; SULFURIC ACID 10 [hp_X]/1 mL; VERBASCUM THAPSUS 10 [hp_X]/1 mL; VIPERA BERUS VENOM 10 [hp_X]/1 mL; ARNICA MONTANA 10 [hp_X]/1 mL
INACTIVE INGREDIENTS: ALCOHOL; WATER

Swimmers 2526L

INDICATIONS & USAGE SECTION

Formulated for associated symptoms such as cramping, dry skin, fatigue, muscle soreness and for the exposure to pool chemicals.

DOSAGE & ADMINISTRATION SECTION

Directions: Ages 12 and up, take 6 drops by mouth (ages 0 to 11, give 3 drops) as needed or as directed by a health professional. Sensitive persons begin with 1 drop and gradually increase to full dose.

OTC - ACTIVE INGREDIENT SECTION

Equal parts of Antimonium tartaricum 10x, Arnica montana 10x, Bellis perennis 10x, Bryonia 10x, Calcarea carbonica 10x, Capsicum annuum 10x, Chelidonium majus 10x, Cuprum metallicum 10x, Digitalis purpurea 10x, Drosera 10x, Lachesis mutus 10x, Lacticum acidum 10x, Ledum palustre 10x, Magnesia carbonica 10x, Manganum aceticum 10x, Nux vomica 10x,Phytolacca decandra 10x, Rhus toxicodendron 10x, Ruta graveolens 10x, Sarcolacticum acidum 10x, Sulphuricum acidum 10x, Verbascum thapsus 10x, Vipera berus 10x.

OTC - PURPOSE SECTION

Formulated for associated symptoms such as cramping, dry skin, fatigue, muscle soreness and for the exposure to pool chemicals.

INACTIVE INGREDIENT SECTION

Inactive Ingredients: USP Purified Water; USP Gluten-free, non-GMO, organic cane alcohol 20%

QUESTIONS SECTION

newtonlabs.net - Questions? 800.448.7256

Newton Laboratories, Inc. FDA Est # 1051203 Conyers, GA 30013

WARNINGS SECTION

WARNINGS: Keep out of reach of children. Do not use if tamper-evident seal is broken or missing. If symptoms worsen or persist for more than a few days, consult a doctor. If pregnant or breast-feeding, ask a doctor before use.

OTC - PREGNANCY OR BREAST FEEDING SECTION

If pregnant or breast-feeding, ask a doctor before use.

OTC - KEEP OUT OF REACH OF CHILDREN SECTION

Keep out of reach of children.